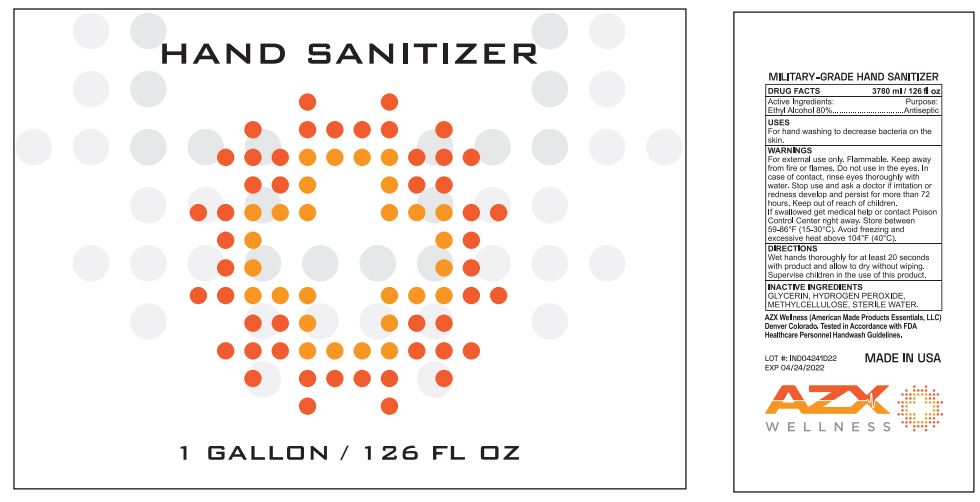 DRUG LABEL: AZX Wellness Hand Sanitizer
NDC: 73145-007 | Form: GEL
Manufacturer: ASC Marketing LTD
Category: otc | Type: HUMAN OTC DRUG LABEL
Date: 20231201

ACTIVE INGREDIENTS: ALCOHOL 0.8 mL/1 mL
INACTIVE INGREDIENTS: GLYCERIN; HYDROGEN PEROXIDE; METHYLCELLULOSE, UNSPECIFIED; WATER

AZX Wellness Hand Sanitizer

Active Ingredients:

Ethyl Alcohol 80%

Purpose:

Antiseptic

USES

For hand washing to decrease bacteria on the skin.

WARNINGS

For external use only. Flammable. Keep away from fire or flames.

Do not use

in the eyes. In case of contact, rinse eyes thoroughly with water.

Stop use and ask a doctor

if irritation or redness develop and persist for more than 72 hours.

Keep out of reach of children.

If swallowed get medical help or contact Poison Control Center right away. Store between 59-86°F (15-30°C). Avoid freezing and excessive heat above 104°F (40°C).

DIRECTIONS

Wet hands thoroughly for at least 20 seconds with product and allow to dry without wiping. Supervise children in the use of this product.

INACTIVE INGREDIENTS

GLYCERIN, HYDROGEN PEROXIDE, METHYLCELLULOSE, STERILE WATER.